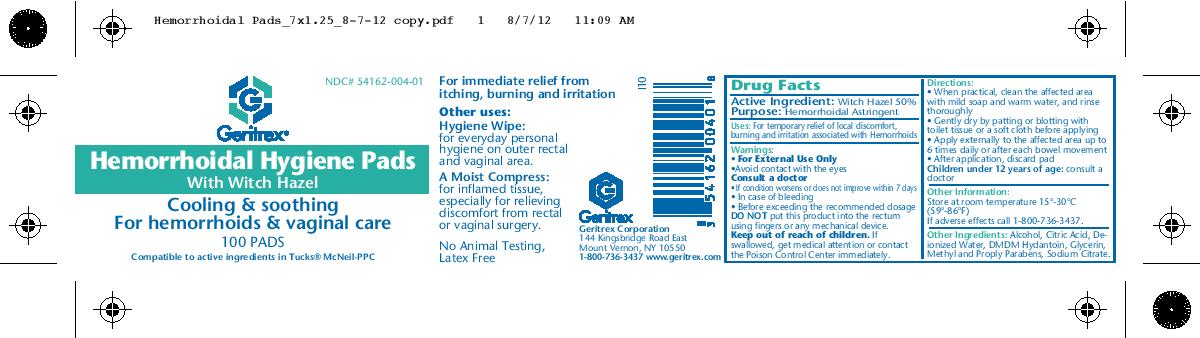 DRUG LABEL: Hemorrhoidal Hygiene pads
NDC: 54162-004 | Form: SOLUTION
Manufacturer: Geritrex, LLC
Category: otc | Type: HUMAN OTC DRUG LABEL
Date: 20181224

ACTIVE INGREDIENTS: WITCH HAZEL 50 g/100 mL
INACTIVE INGREDIENTS: ALCOHOL; ACETYLTRIBUTYL CITRATE; WATER; GLYCERIN; SODIUM CITRATE; DMDM HYDANTOIN

Hemrrhoidal Hygiene pads

Drug Facts

Witch Hazel 50%
Purpose: Hemorrhoidal Astringent

Uses

For temporary relief of local discomfort,
burning and irritation associated with Hemorrhoids

Directions

When practical, clean the affected area
with mild soap and warm water, and rinse
thoroughly
• Gently dry by patting or blotting with
toilet tissue or a soft cloth before applying
• Apply externally to the affected area up to
6 times daily or after each bowel movement
• After application, discard pad
Children under 12 years of age: consult a
doctor

DOSAGE AND ADMINISTRATION

Apply externally to the affected area up to
6 times daily or after each bowel movement

WARNINGS

• For External Use Only
•Avoid contact with the eyes
Consult a doctor
• If condition worsens or does not improve within 7 days
• In case of bleeding
• Before exceeding the recommended dosage
DO NOT put this product into the rectum
using fingers or any mechanical device.

Other Ingredient

Alcohol, Citric Acid,
Deionized Water, DMDM Hydantoin,
Glycerin, Sodium Citrate.

STORAGE AND HANDLING

Store at room temperature 15°-30°C
(59°-86°F)

KEEP OUT OF REACH OF CHILDREN

If swallowed, contact the Poison Control Center immediately.